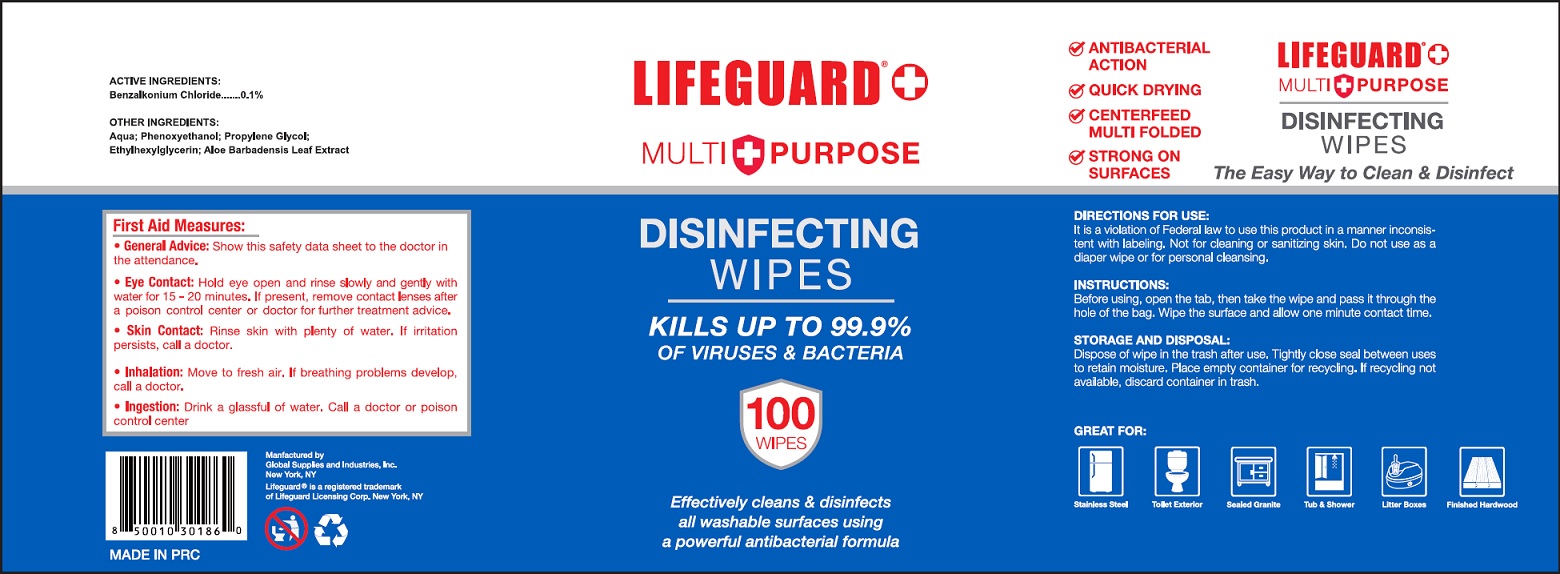 DRUG LABEL: LIFEGUARD DISINFECTING WIPES
NDC: 79680-008 | Form: SWAB
Manufacturer: Zhejiang Saiveroy Cleaning Products Co., LTD.
Category: otc | Type: HUMAN OTC DRUG LABEL
Date: 20201207

ACTIVE INGREDIENTS: BENZALKONIUM CHLORIDE 0.10 g/100 g
INACTIVE INGREDIENTS: WATER; PHENOXYETHANOL; ETHYLHEXYLGLYCERIN; PROPYLENE GLYCOL; ALOE VERA LEAF

Wipes

Active Ingredient

Benzalkonium Chloride 0.10%

Purpose

Antiseptic

USE

Signle use wipes to clean.

Warning

- General Advice: show this safety data sheet to the doctor in the attendance.
- Eye contact: Hold eye open and rinse slowly and gently with water for 15-20 minutes. If preset, remove contact lenses after a poison control center or doctor for further treatment advice.
- Skin Contact: Rinse skin with plenty of water. If irritation persists, call a doctor.
- Inhalation: Move a fresh air. If breathing problems develop, call a doctor.
- Ingestion: Drink a glassful of water. Call a doctor or poison control center.

KEEP OUT OF REACH OF CHILDREN

●If swallowed, get medical help or contact a Poison Contrl Center right away.

Directions for use; Instruction, Storage and Disposal

Directions for use:

It is a violation of Federal law to use this product in a manner inconsistent with labeling. Not for cleaning or sanitizing skin. Do not use as a diaper wipe or for personal cleansing.

Instructions:

Before using, open the tab, then take the wipe and pass it through the hole of the bag. wipe the surface and allow one minute contact time.

Storage and Disposal:

Dispose of wipe in the trash after use. Tightly close seal between uses to retain moisture. Please empty container for recycling. If recycling not available, discard container in trash.

Inactive ingredients

Aqua, Phenoxyethanol, Ethylhexylglycerin, Propylene Glycol, Aloe Barbadensis Leaf Extract.